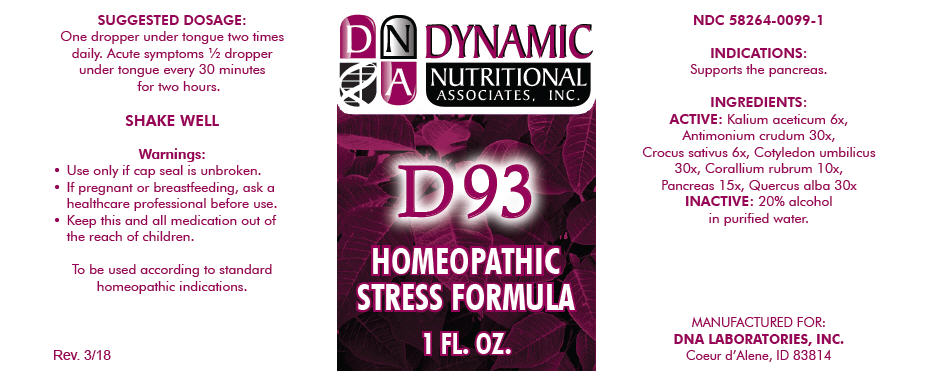 DRUG LABEL: D-93
NDC: 58264-0099 | Form: SOLUTION
Manufacturer: DNA Labs, Inc.
Category: homeopathic | Type: HUMAN OTC DRUG LABEL
Date: 20250113

ACTIVE INGREDIENTS: POTASSIUM ACETATE 6 [hp_X]/1 mL; ANTIMONY TRISULFIDE 30 [hp_X]/1 mL; SAFFRON 6 [hp_X]/1 mL; UMBILICUS RUPESTRIS 30 [hp_X]/1 mL; CORALLIUM RUBRUM EXOSKELETON 10 [hp_X]/1 mL; BOS TAURUS PANCREAS 15 [hp_X]/1 mL; QUERCUS ALBA WOOD 30 [hp_X]/1 mL
INACTIVE INGREDIENTS: ALCOHOL; WATER

D-93

NDC 58264-0099-1

INDICATIONS

PURPOSE

Supports the pancreas.

INGREDIENTS

ACTIVE

Kalium aceticum 6x, Antimonium crudum 30x, Crocus sativus 6x, Cotyledon umbilicus 30x, Corallium rubrum 10x, Pancreas 15x, Quercus alba 30x

INACTIVE

20% alcohol in purified water.

SUGGESTED DOSAGE

One dropper under tongue two times daily. Acute symptoms ½ dropper under tongue every 30 minutes for two hours.

STORAGE AND HANDLING

SHAKE WELL

Warnings

- Use only if cap seal is unbroken.

PREGNANCY OR BREAST FEEDING

- If pregnant or breastfeeding, ask a healthcare professional before use.

KEEP OUT OF REACH OF CHILDREN

- Keep this and all medication out of the reach of children.

To be used according to standard homeopathic indications.

PRINCIPAL DISPLAY PANEL - 1 FL. OZ. Bottle Label

DYNAMIC
NUTRITIONAL
ASSOCIATES, INC.

D 93

HOMEOPATHIC
STRESS FORMULA

1 FL. OZ.